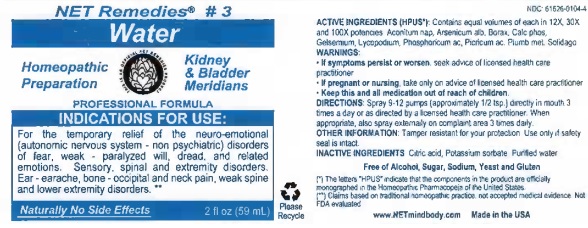 DRUG LABEL: Water
NDC: 61626-0104 | Form: LIQUID
Manufacturer: NET Remedies
Category: homeopathic | Type: HUMAN OTC DRUG LABEL
Date: 20210119

ACTIVE INGREDIENTS: ACONITUM NAPELLUS 12 [hp_X]/59 mL; ARSENIC TRIOXIDE 12 [hp_X]/59 mL; SODIUM BORATE 12 [hp_X]/59 mL; TRIBASIC CALCIUM PHOSPHATE 12 [hp_X]/59 mL; GELSEMIUM SEMPERVIRENS ROOT 12 [hp_X]/59 mL; LYCOPODIUM CLAVATUM SPORE 12 [hp_X]/59 mL; PHOSPHORIC ACID 12 [hp_X]/59 mL; PICRIC ACID 12 [hp_X]/59 mL; LEAD 12 [hp_X]/59 mL; SOLIDAGO VIRGAUREA FLOWERING TOP 12 [hp_X]/59 mL
INACTIVE INGREDIENTS: CITRIC ACID MONOHYDRATE; POTASSIUM SORBATE; WATER

Water

ACTIVE INGREDIENT

ACTIVE INGREDIENTS (HPUS*): Contains equal volumes of each in 12X, 30X, and 100X potencies: Aconitum nap, Arsenicum alb, Borax, Calc phos, Gelsenium, Lycopodium, Phosphoricum ac, Picricum ac, Plumb met, Solidago

(*) The letters "HPUS" indicate that the components in the product are officially monographed in the Homeopathic Pharmacopoeia of the Unites States.

(**) Claims based on traditional homeopathic practice, not accepted medical evidence. Not FDA evaluated.

INDICATIONS AND USAGE

INDICATIONS FOR USE: For the temporary relief of the neuro-emotional (autonomic nervous system - non psychiatric) disorders of fear, weak - paralyzed will, dread, and related emotions. Sensory, spinal and extremity disorders. Ear - earache, bone - occipital and neck pain, weak spine and lower extremity disorders.**

WARNINGS:

• If symptoms persist or worsen, seek advice of licensed health care practicioner.

• If pregnant or nursing, take only on advice of licensed health care practicioner.

• Keep this and all medication out of reach of children.

KEEP OUT OF REACH OF CHILDREN

• Keep this and all medication out of reach of children.

DOSAGE AND ADMINISTRATION

DIRECTIONS: Spray 9-12 pumps (approximately 1/2 tsp.) directly in mouth 3 times a day or as directed by a licensed health care practitioner. When approprate, also spray externally on complaint area 3 times daily.

OTHER INFORMATION: Tamper resistant for your protection. Use only if safetly seal is intact.

INACTIVE INGREDIENTS: Citric acid, Potassium sorbate, Purified water.

Free of Alcohol, Sugar, Sodium, Yeast and Gluten.

QUESTIONS

www.NETmindbody.com

Made in the USA.

PACKAGE LABEL

NET Remedies #3

Water

Homeopathic preparation

Kidney & Bladder Meridians

Naturally No Side Effects

2 fl oz (59 mL)

PURPOSE

For the temporary relief of the neuro-emotional (autonomic nervous system - non psychiatric) disorders of fear, weak - paralyzed will, dread, and related emotions. Sensory, spinal and extremity disorders. Ear - earache, bone - occipital and neck pain, weak spine and lower extremity disorders.**